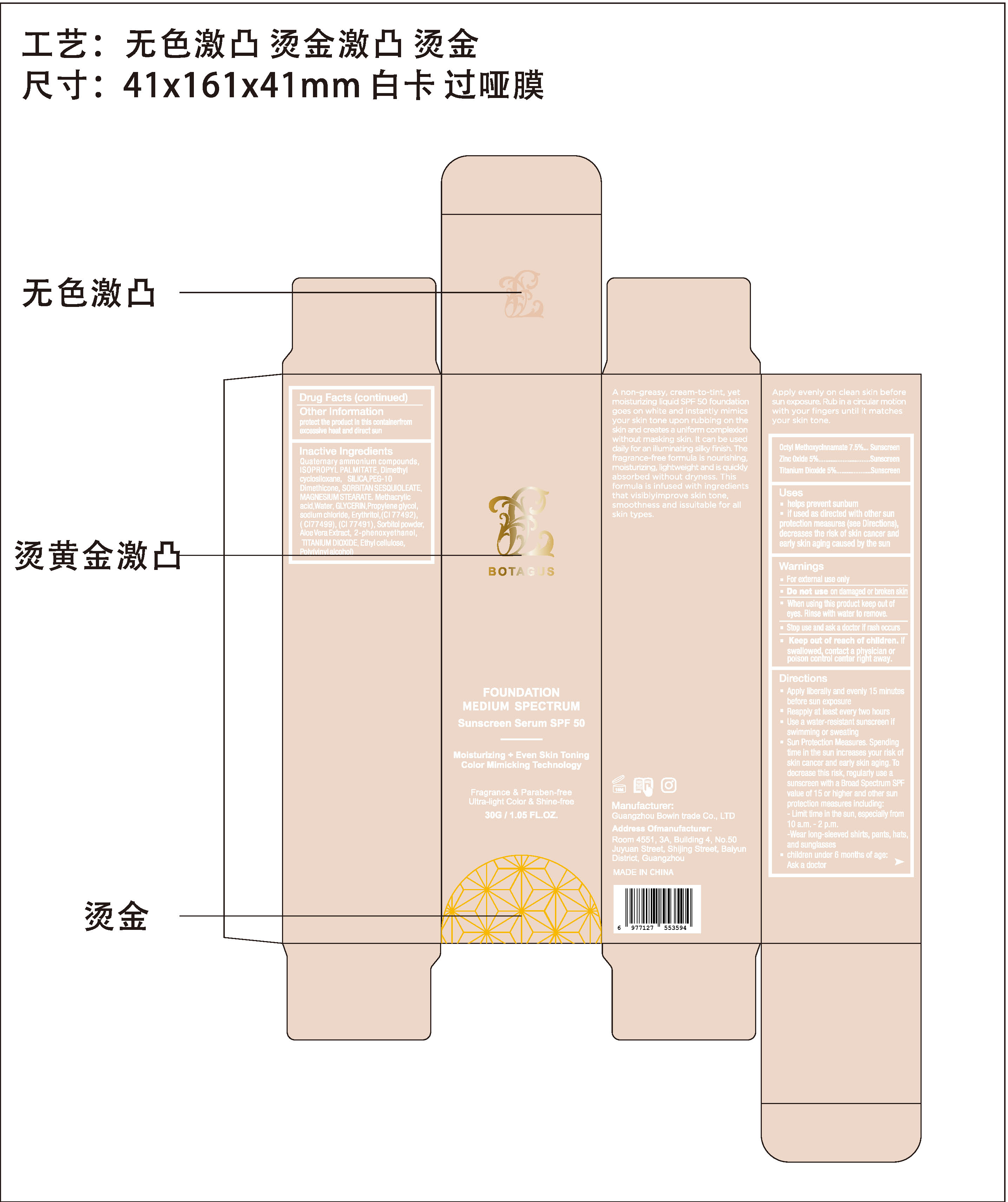 DRUG LABEL: FOUNDATION MEDIUM SPECTRUM
NDC: 84958-002 | Form: LIQUID
Manufacturer: Guangzhou Bo win Trade Co., Ltd.
Category: otc | Type: HUMAN OTC DRUG LABEL
Date: 20241119

ACTIVE INGREDIENTS: ZINC OXIDE 5 g/100 g; OCTINOXATE 7.5 g/100 g; TITANIUM DIOXIDE 5 g/100 g
INACTIVE INGREDIENTS: CYCLOMETHICONE; PEG-10 DIMETHICONE (900 CST); CI 77492; SODIUM CHLORIDE; SILICA; METHACRYLIC ACID; WATER; ETHYLCELLULOSE, UNSPECIFIED; POLYVINYL ALCOHOL, UNSPECIFIED; ISOPROPYL PALMITATE; CI 77499; CI 77491; ERYTHRITOL; ALOE VERA LEAF EXTRACT; SORBITOL; GLYCERIN; PHENOXYETHANOL; C8-10 TRIALKYLMETHYL QUATERNARY AMMONIUM CHLORIDES; SORBITAN SESQUIOLEATE; MAGNESIUM STEARATE; PROPYLENE GLYCOL

FOUNDATION MEDIUM SPECTRUM

ACTIVE INGREDIENT

Octyl Methoxycinnamate 7.5%
Zinc Oxide 5%
Titanium Dioxide 5%

PURPOSE

Sunscreen

Keep out of reach of children.

lf swallowed, contact a physician orpoison control center right away.

INDICATIONS AND USAGE

helps prevent sunbum

if used as directed with other sunprotection measures (see Directions)decreases the risk of skin cancer andearly skin aging caused by the sun

WARNINGS

For external use only

When using this product keep out ofeyes. Rinse with water to remove.

Do not use on damaged or broken skin

Stop use and ask a doctor if rash occurs

DOSAGE AND ADMINISTRATION

Apply liberally and evenly 15 minutesbefore sun exposure
Reapply at least every two hours
Use a water-resistant sunscreen ifswimming or sweating
Sun Protection Measures. Spendingtime in the sun increases your risk ofskin cancer and early skin aging.Todecrease this risk, regularly use asunscreen with a Broad Spectrum SPFvalue of 15 or higher and other sunprotection measures including:- Limit time in the sun, especially from10 a.m.- 2 p.m.-Wear long-sleeved shirts, pants, hatsand sunglasses
children under 6 months of age:Ask a doctor

INACTIVE INGREDIENT

Quaternary ammonium compounds
ISOPROPYL PALMITATE
Dimethyl cyclosiloxane
SILICA
PEG-10 Dimethicone
SORBITAN SESQUIOLEATE
MAGNESIUM STEARATE
Methacrylic acid
WATER
GLYCERIN
Propylene glycol
sodium chloride
Erythritol
CI 77492
CI 77491
CI 77499
Sorbitol powder
Aloe Vera Extract
2-phenoxyethanol
Poly(vinyl alcohol)
Ethyl cellulose